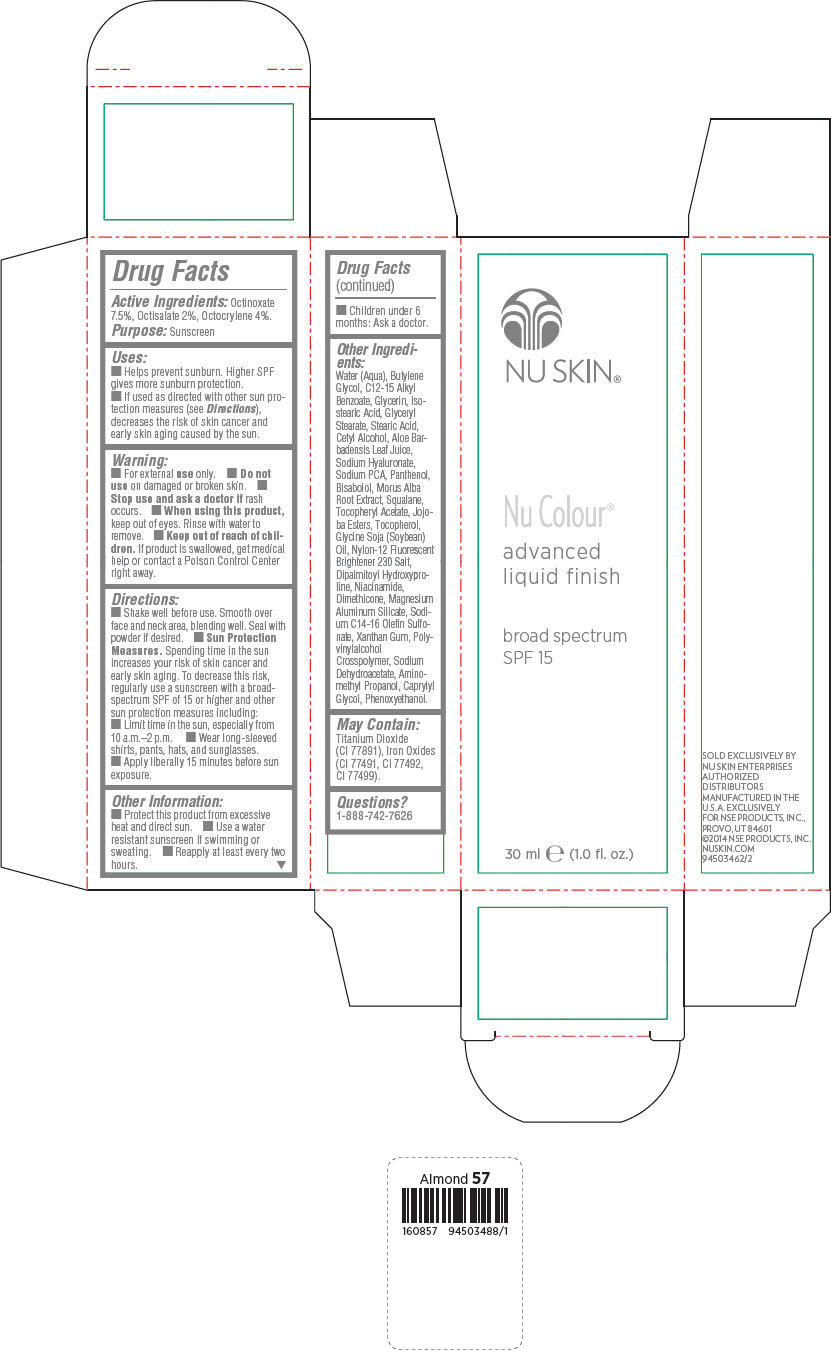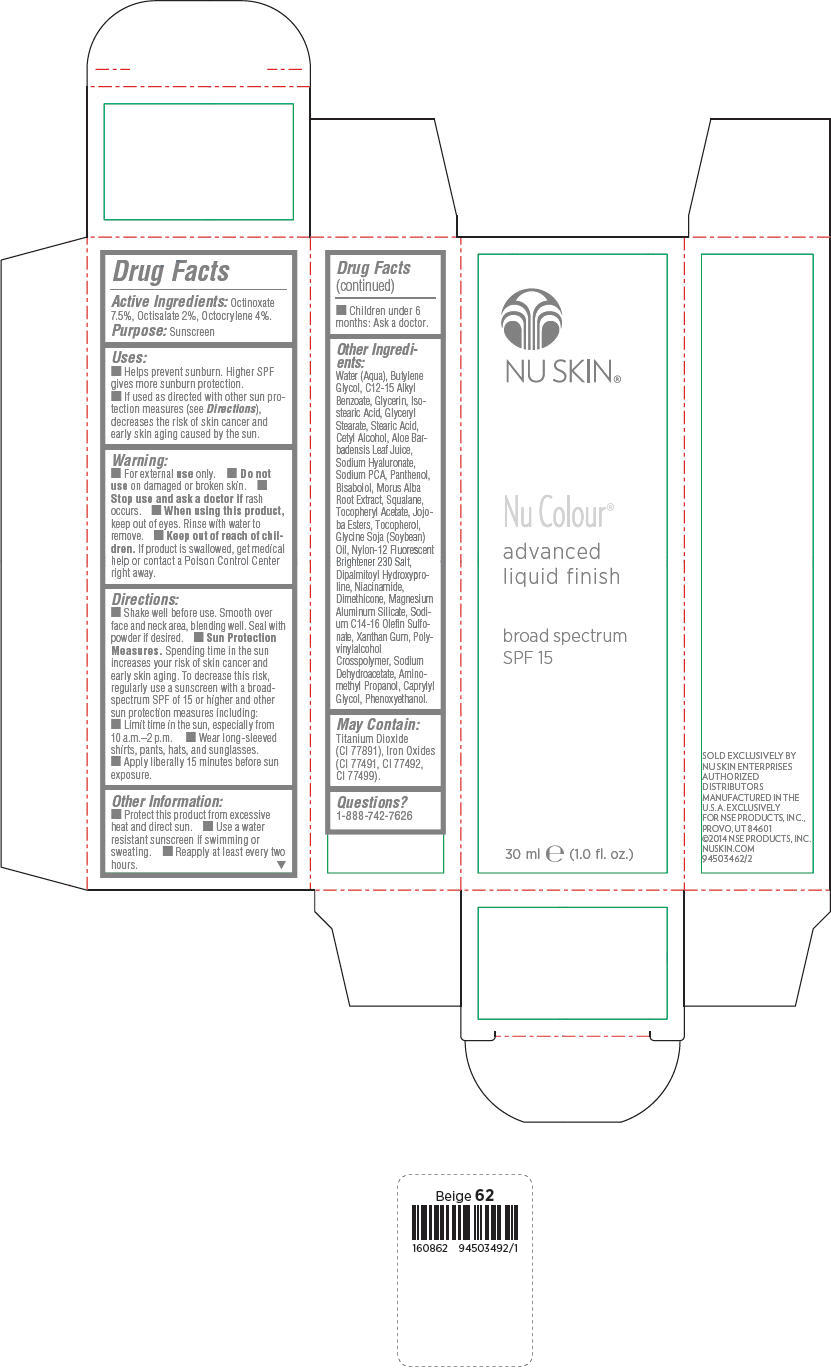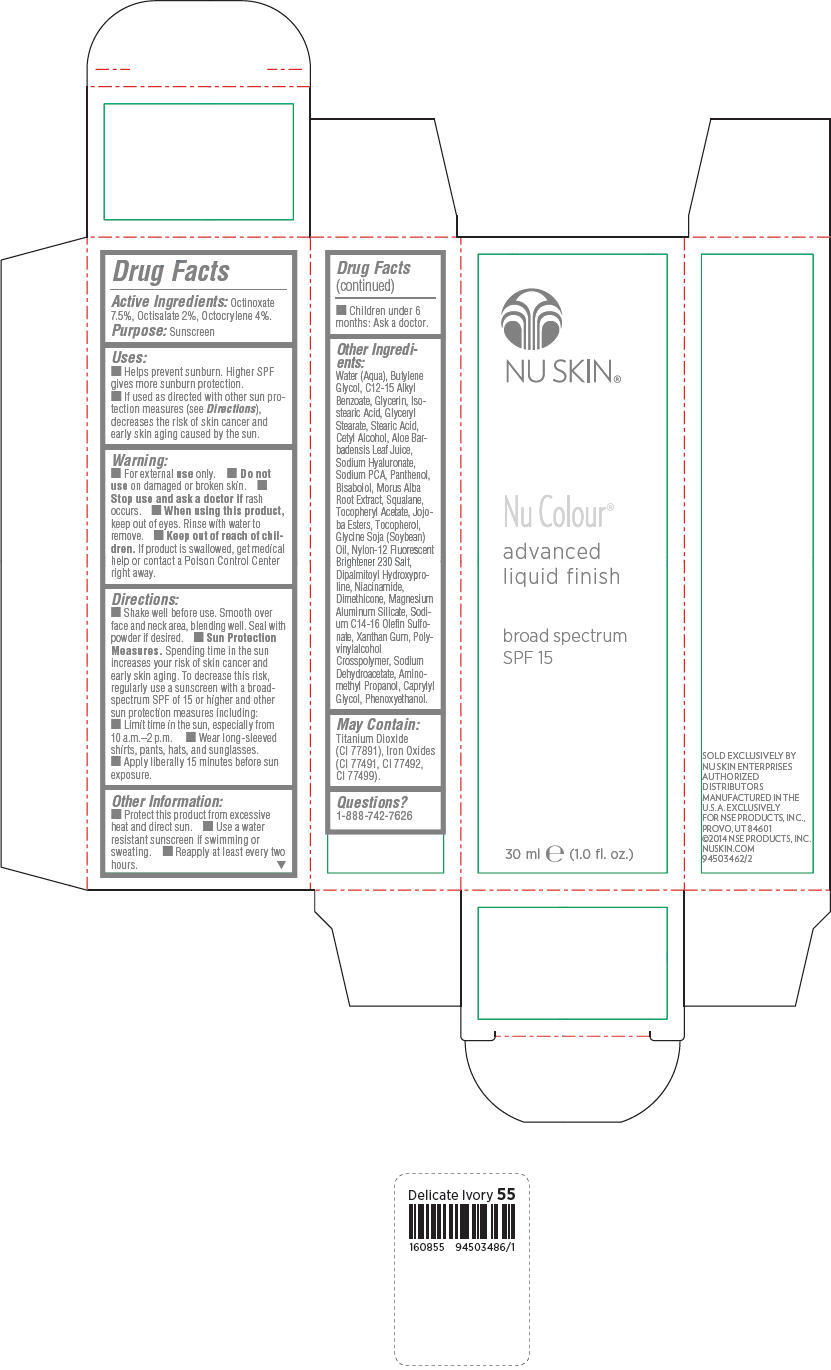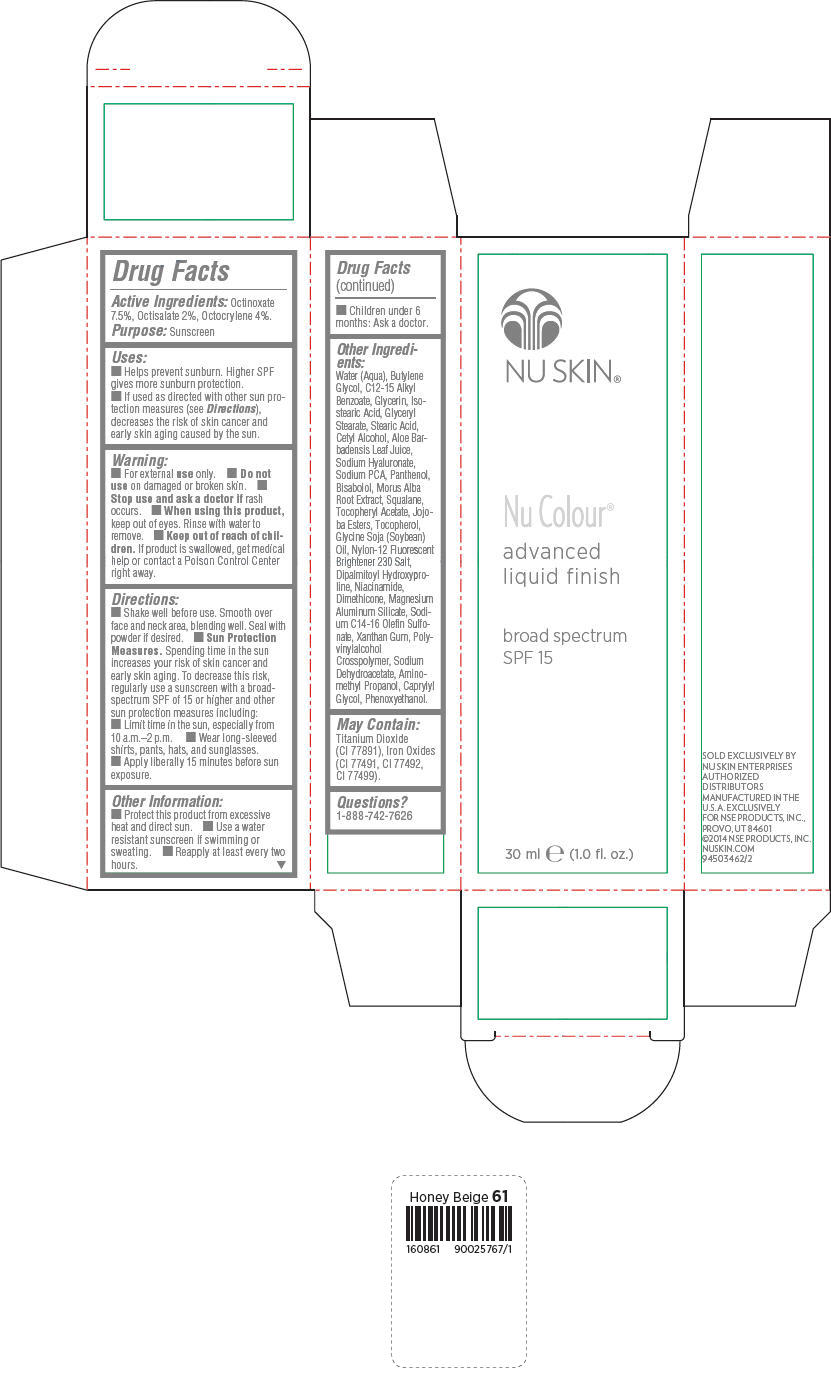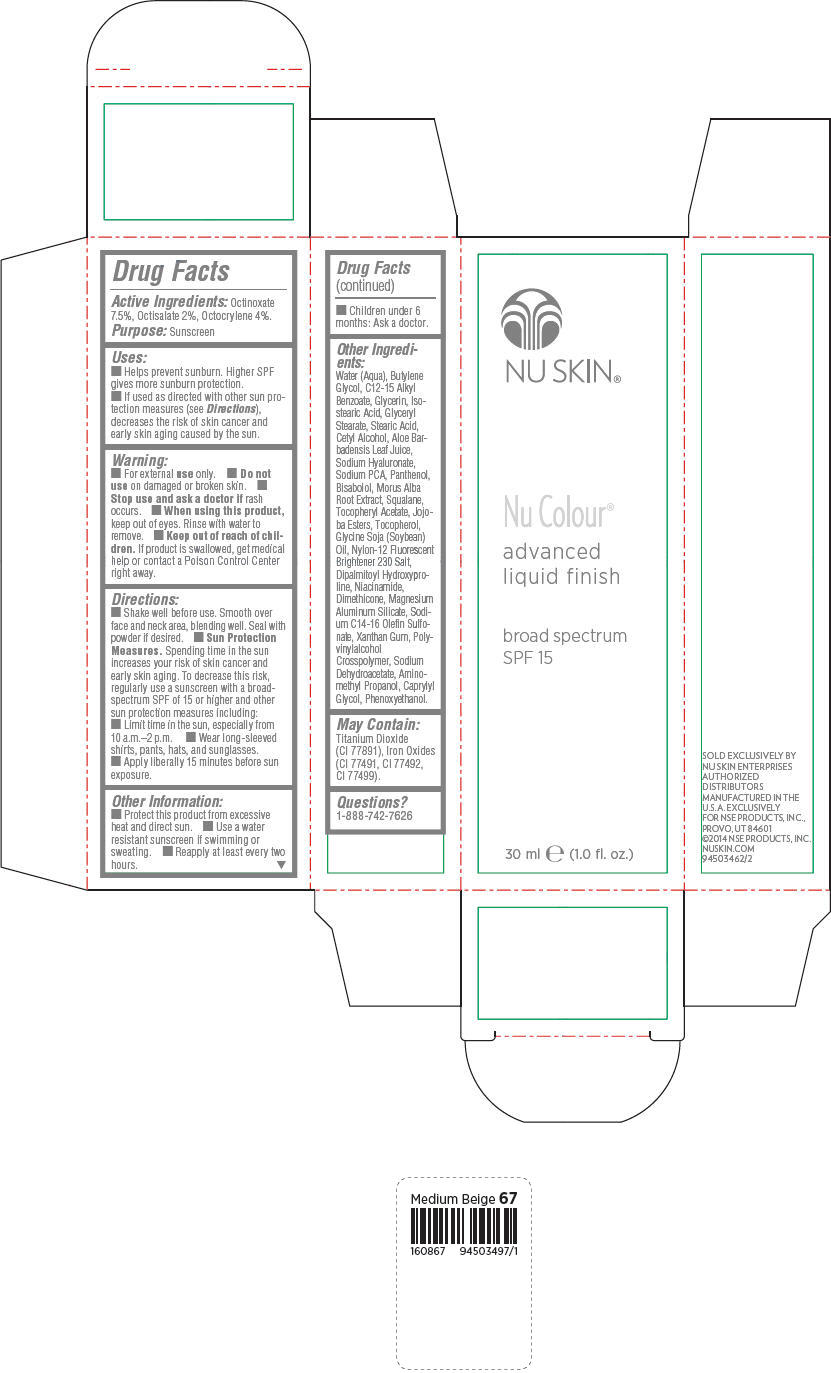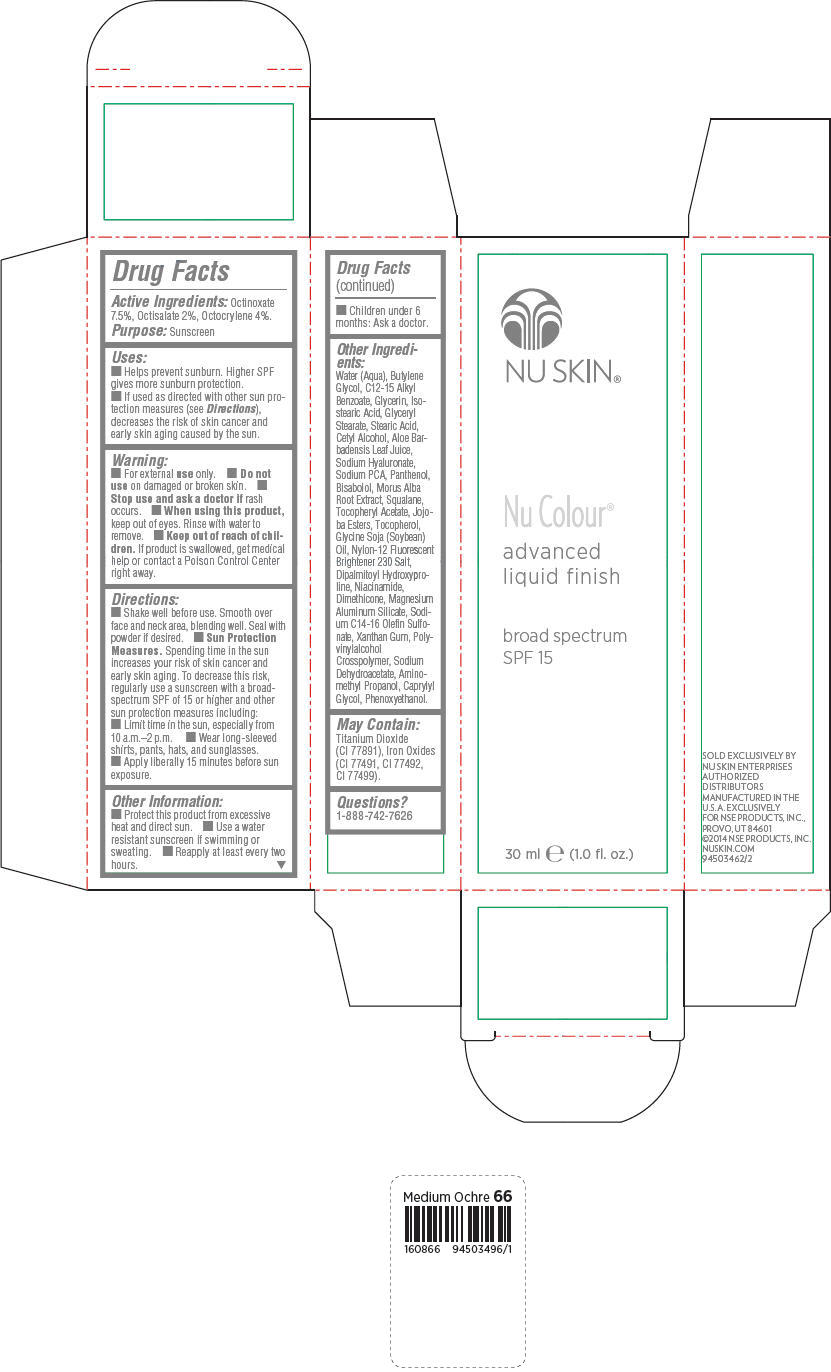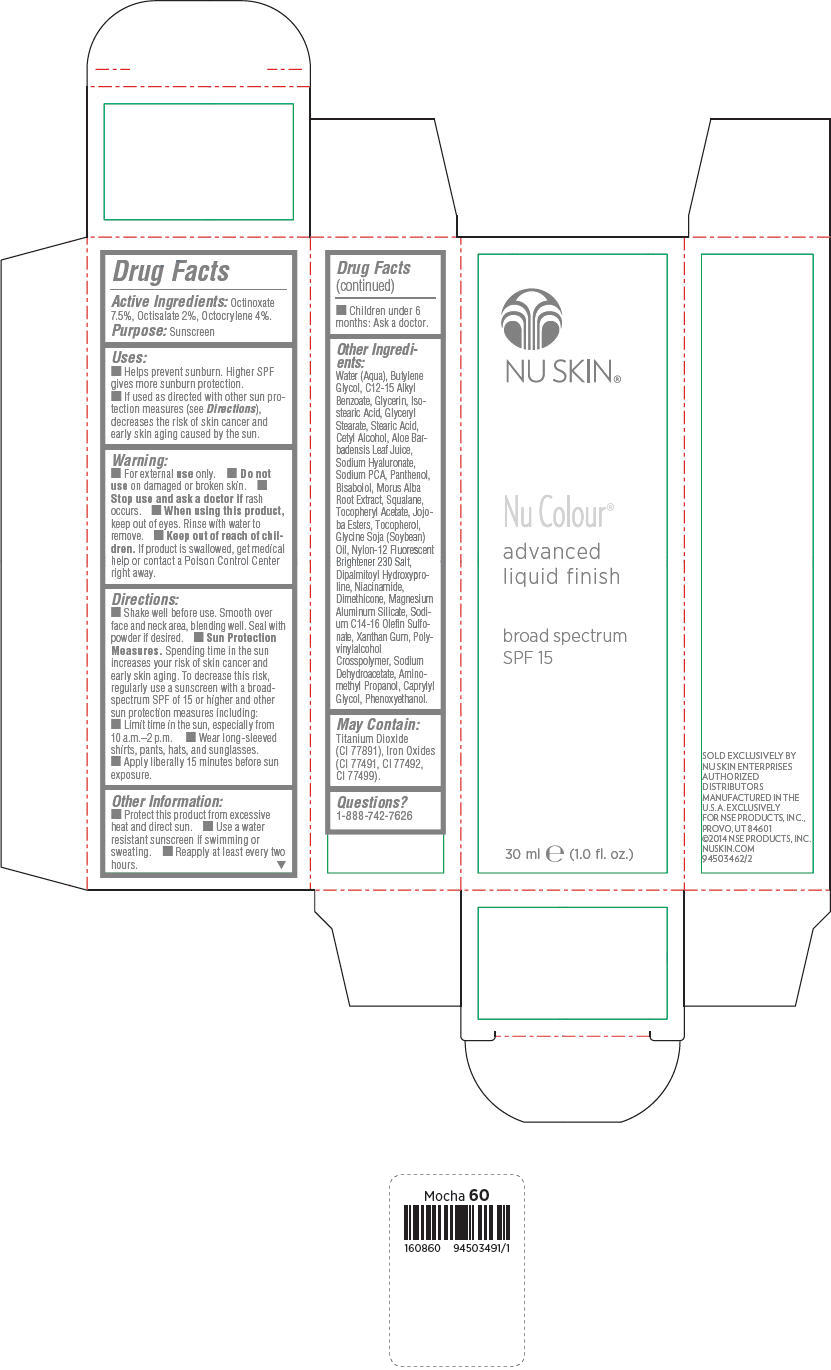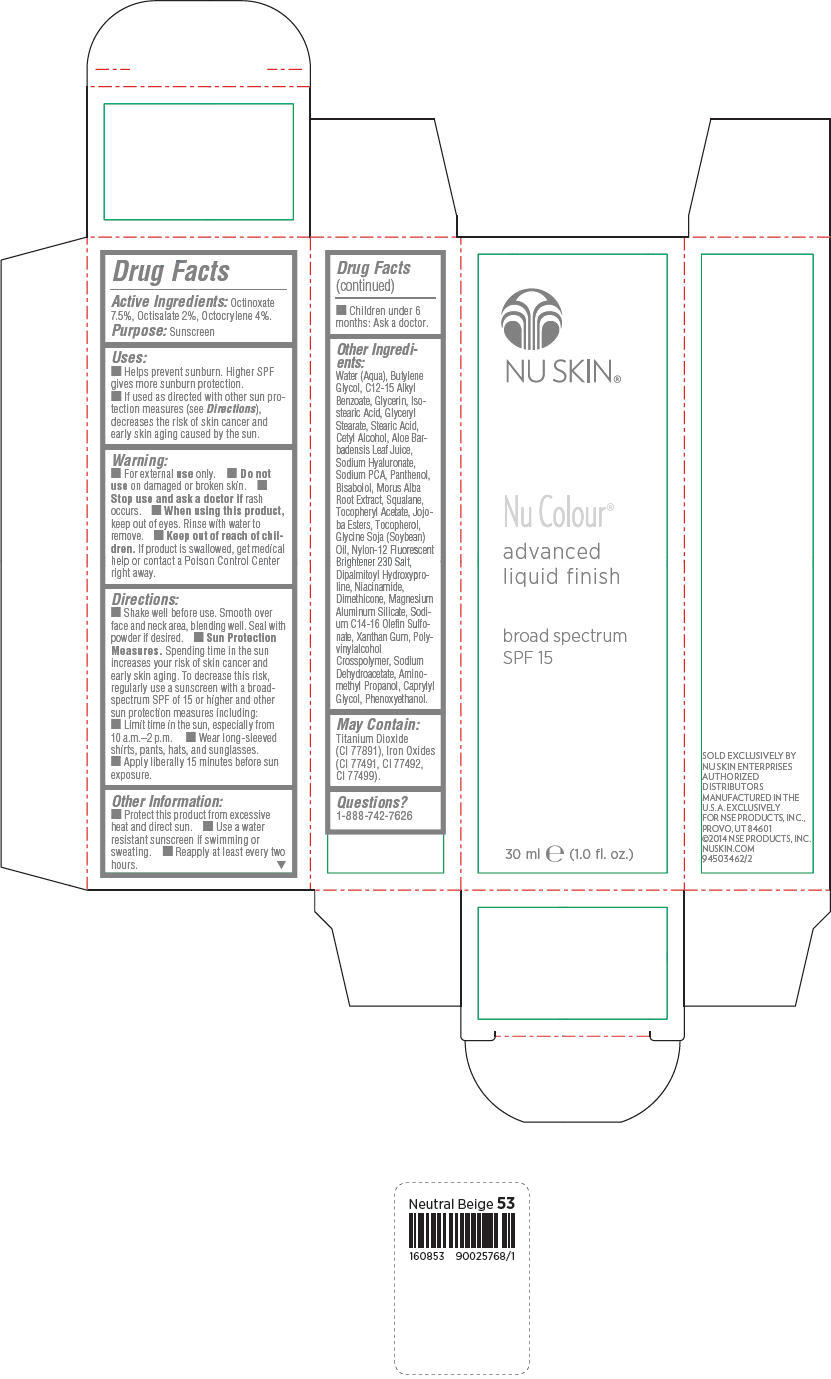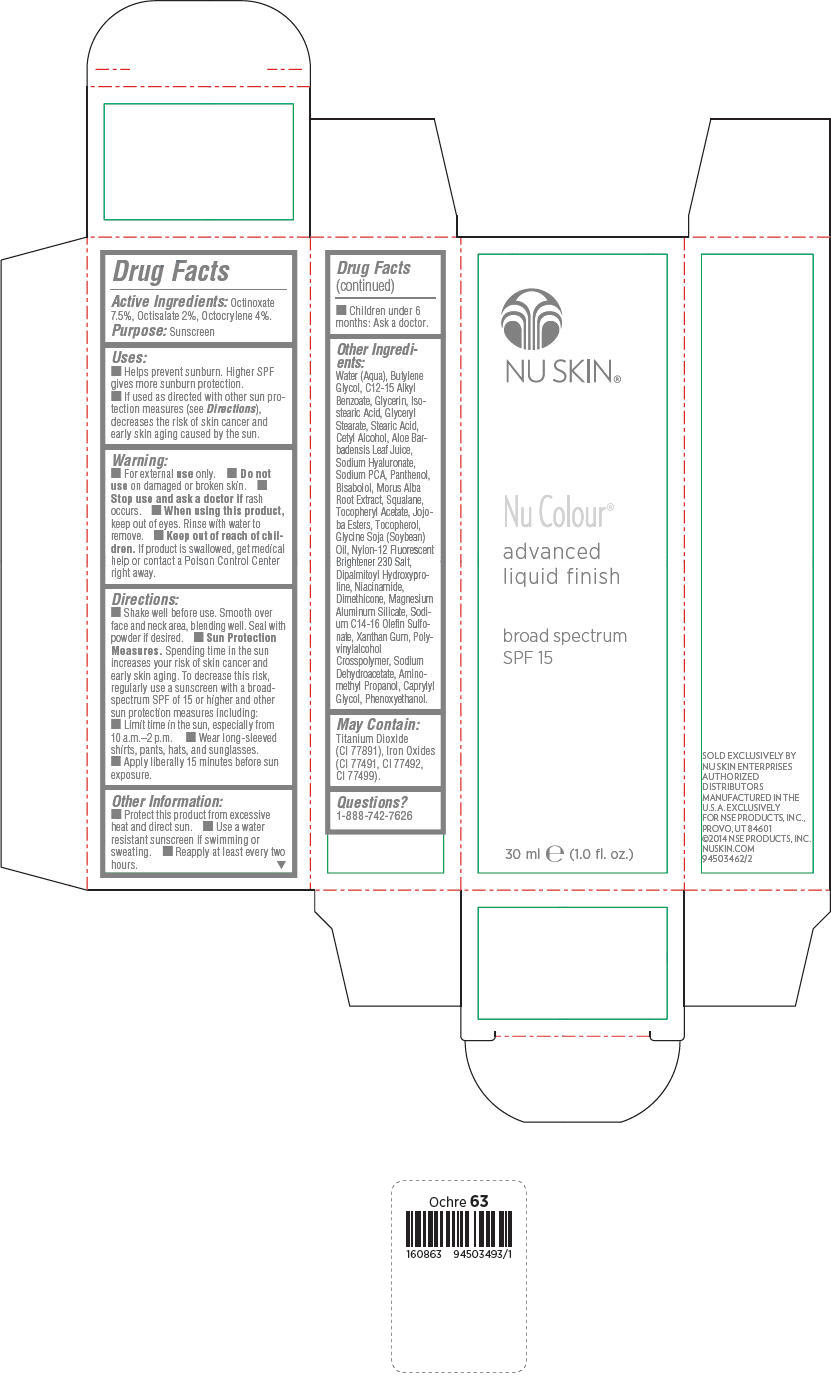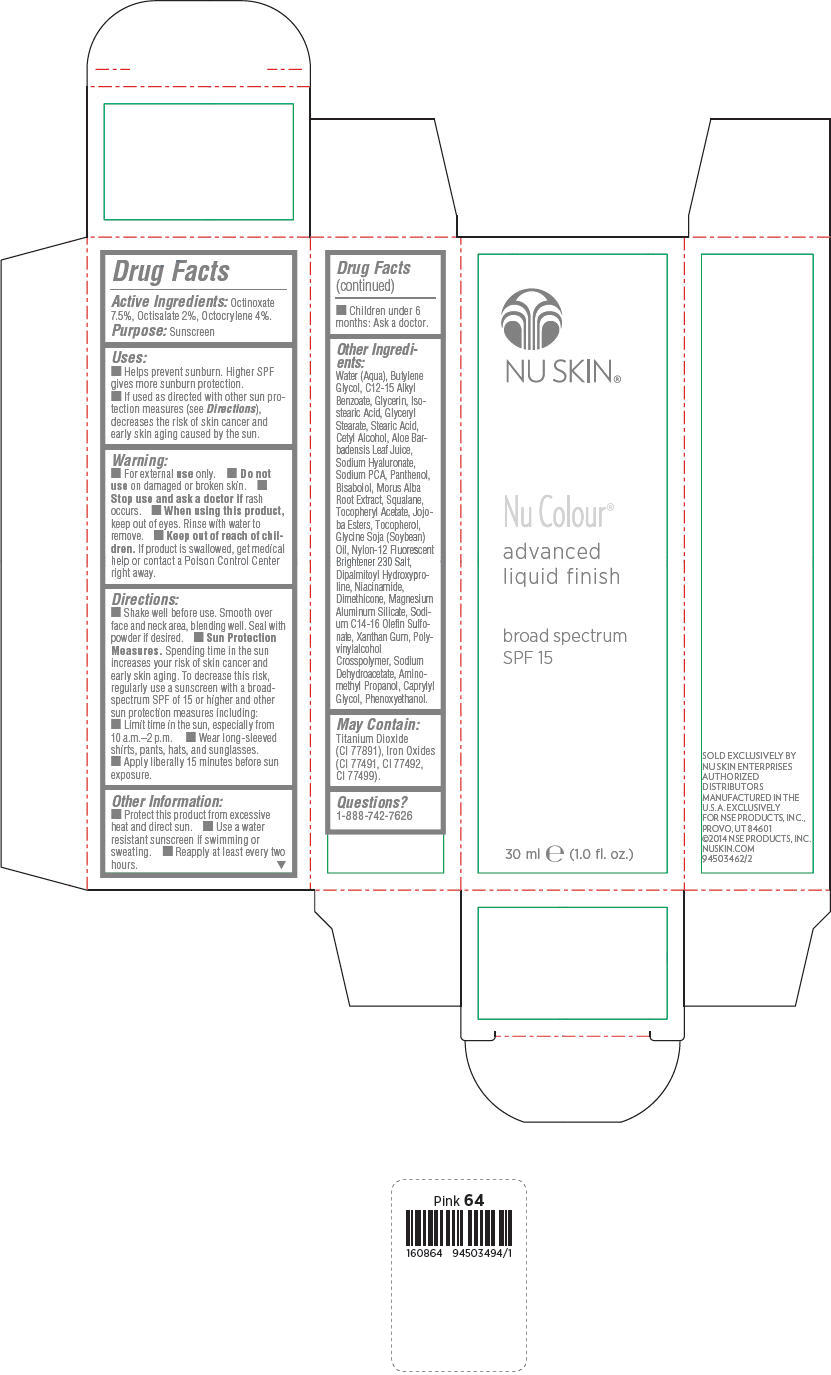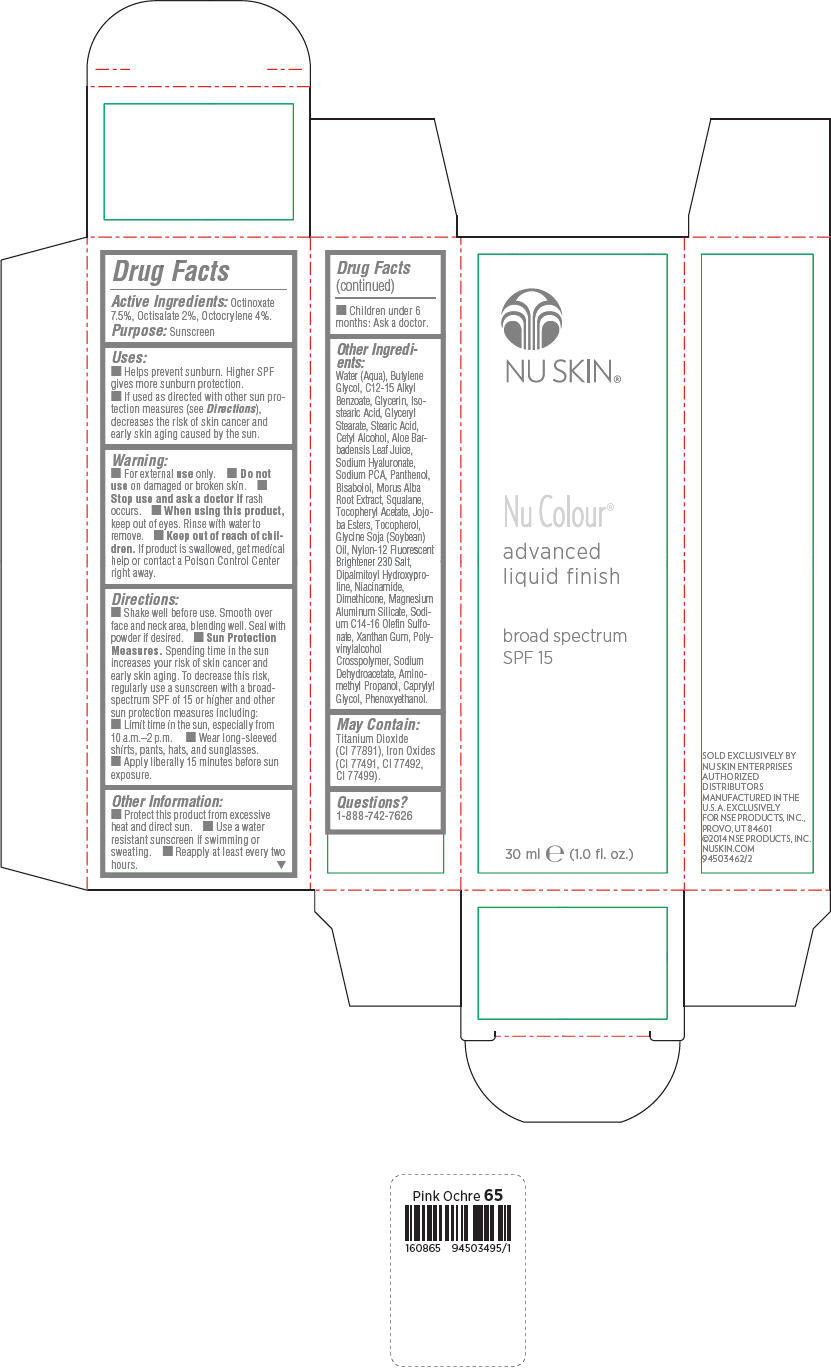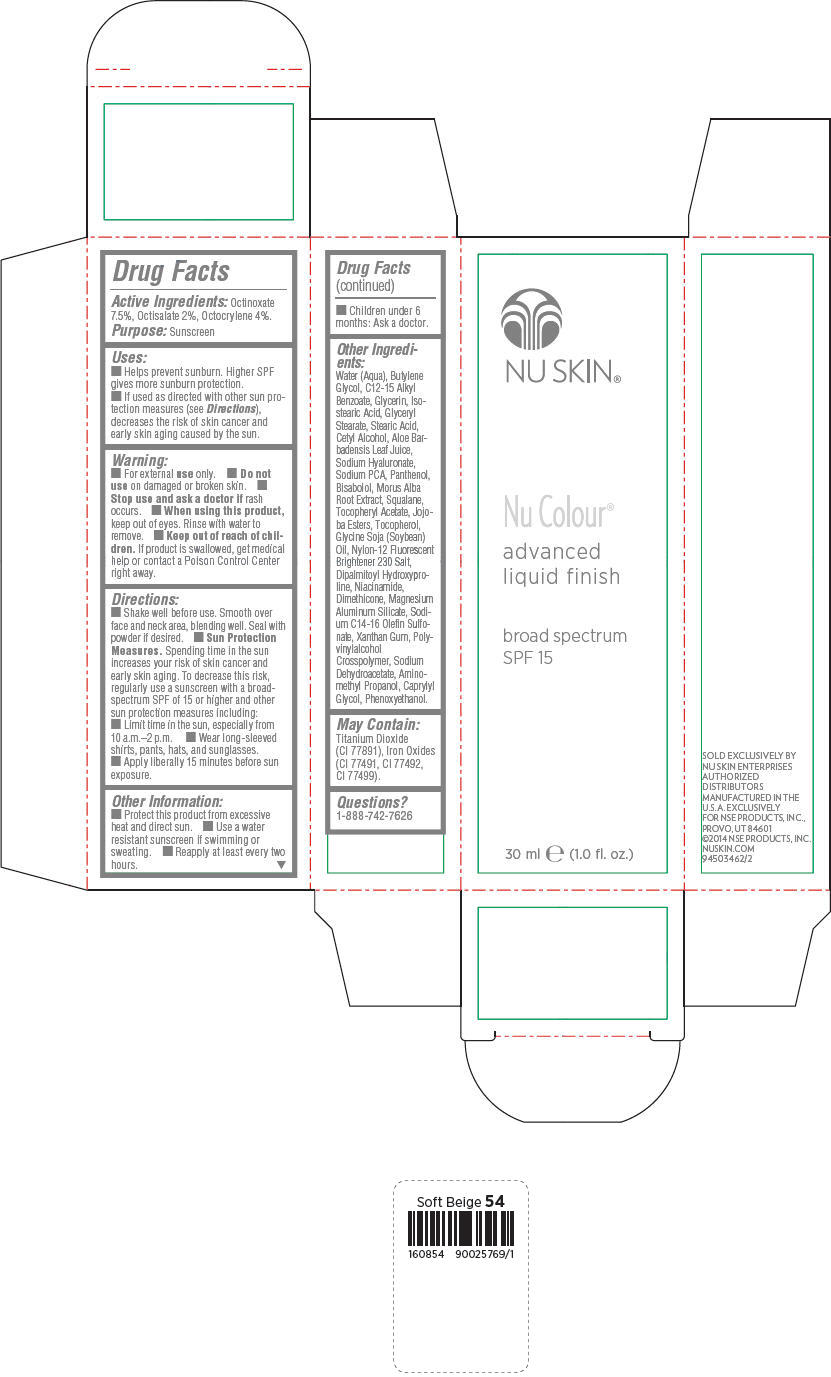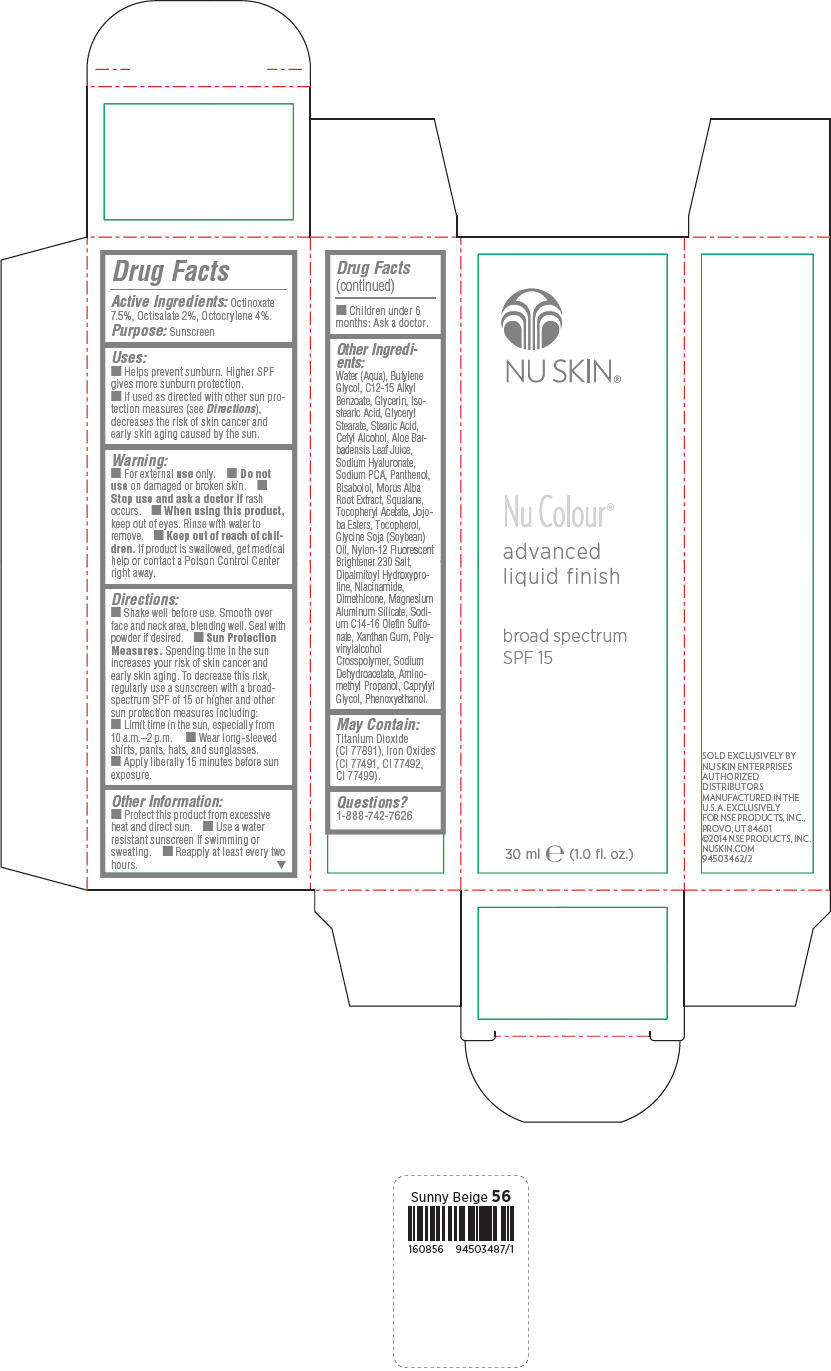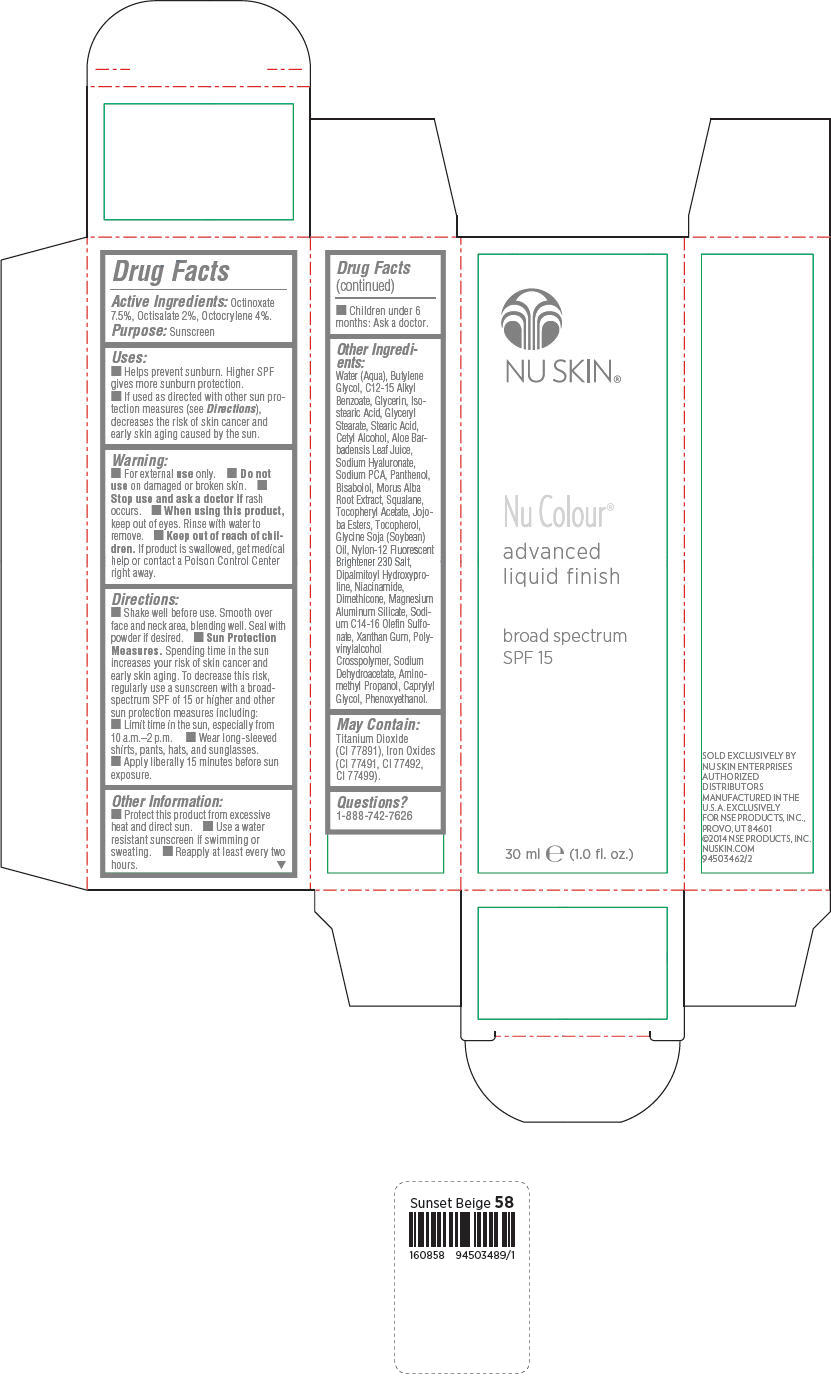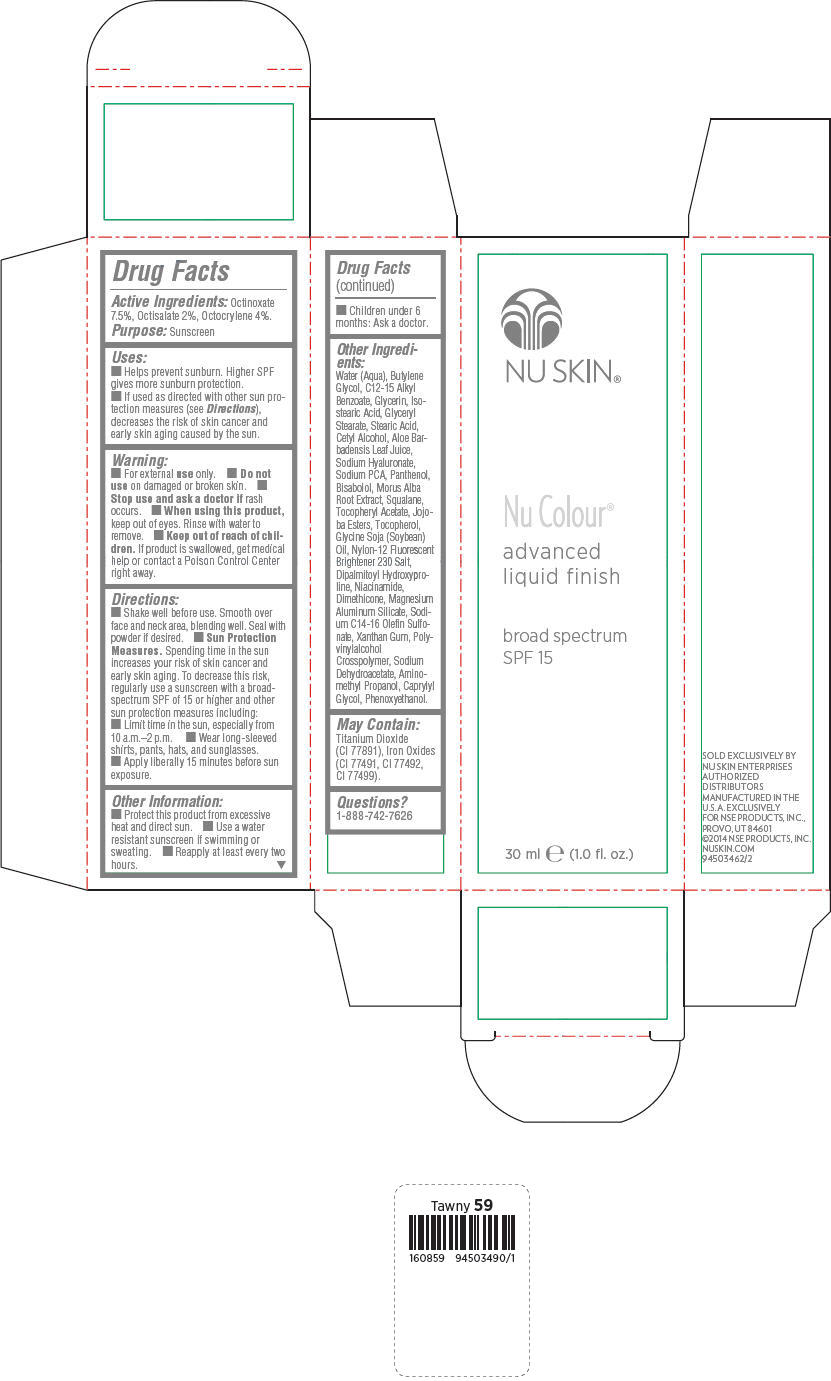 DRUG LABEL: Nu Skin Nu Colour advanced finish broad spectrum SPF 15 - Almond
NDC: 62839-0857 | Form: LOTION
Manufacturer: NSE Products, Inc.
Category: otc | Type: HUMAN OTC DRUG LABEL
Date: 20191226

ACTIVE INGREDIENTS: Octinoxate 75 mg/1 mL; Octisalate 20 mg/1 mL; Octocrylene 40 mg/1 mL
INACTIVE INGREDIENTS: Water; Butylene Glycol; Alkyl (C12-15) Benzoate; Titanium Dioxide; Glycerin; Isostearic Acid; Glyceryl Monostearate; Stearic Acid; Cetyl Alcohol; Aloe Vera Leaf; Hyaluronate Sodium; Sodium Pyrrolidone Carboxylate; Panthenol; Levomenol; Morus Alba Root; Squalane; .Alpha.-Tocopherol Acetate; Tocopherol; Soybean Oil; Dipalmitoyl Hydroxyproline; Niacinamide; Dimethicone; Magnesium Aluminum Silicate; Sodium C14-16 Olefin Sulfonate; Xanthan Gum; Sodium Dehydroacetate; Aminomethylpropanol; Caprylyl Glycol; Phenoxyethanol; Ferric Oxide Yellow; Ferric Oxide Red; Ferrosoferric Oxide

Nu Skin® Nu Colour® advanced liquid finish broad spectrum SPF 15

Drug Facts

Active Ingredients

Octinoxate 7.5%, Octisalate 2%, Octocrylene 4%.

Purpose

Sunscreen

Uses

- Helps prevent sunburn. Higher SPF gives more sunburn protection.
- If used as directed with other sun protection measures (see Directions), decreases the risk of skin cancer and early skin aging caused by the sun.

Warning

- For external use only.

- Do not use on damaged or broken skin.

- Stop use and ask a doctor if rash occurs.

- When using this product, keep out of eyes. Rinse with water to remove.

- Keep out of reach of children. If product is swallowed, get medical help or contact a Poison Control Center right away.

Directions

- Shake well before use. Smooth over face and neck area, blending well. Seal with powder if desired.
- Sun Protection Measures. Spending time in the sun increases your risk of skin cancer and early skin aging. To decrease this risk, regularly use a sunscreen with a broadspectrum SPF of 15 or higher and other sun protection measures including:
  - Limit time in the sun, especially from 10 a.m.–2 p.m.
  - Wear long-sleeved shirts, pants, hats, and sunglasses.
  - Apply liberally 15 minutes before sun exposure.

Other Information

- Protect this product from excessive heat and direct sun.
- Use a water resistant sunscreen if swimming or sweating.
- Reapply at least every two hours.
- Children under 6 months: Ask a doctor.

Other Ingredients

Water (Aqua), Butylene Glycol, C12-15 Alkyl Benzoate, Glycerin, Isostearic Acid, Glyceryl Stearate, Stearic Acid, Cetyl Alcohol, Aloe Barbadensis Leaf Juice, Sodium Hyaluronate, Sodium PCA, Panthenol, Bisabolol, Morus Alba Root Extract, Squalane, Tocopheryl Acetate, Jojoba Esters, Tocopherol, Glycine Soja (Soybean) Oil, Nylon-12 Fluorescent Brightener 230 Salt, Dipalmitoyl Hydroxyproline, Niacinamide, Dimethicone, Magnesium Aluminum Silicate, Sodium C14-16 Olefin Sulfonate, Xanthan Gum, Polyvinylalcohol Crosspolymer, Sodium Dehydroacetate, Aminomethyl Propanol, Caprylyl Glycol, Phenoxyethanol.

May Contain

Titanium Dioxide (CI 77891), Iron Oxides (CI 77491, CI 77492, CI 77499).

Questions?

1-888-742-7626

PRINCIPAL DISPLAY PANEL - 30 mL Bottle Carton - Almond

NU SKIN®

Nu Colour®

advanced
liquid finish

broad spectrum
SPF 15

30 ml e (1.0 fl. oz.)

PRINCIPAL DISPLAY PANEL - 30 mL Bottle Carton - Beige

NU SKIN®

Nu Colour®

advanced
liquid finish

broad spectrum
SPF 15

30 ml e (1.0 fl. oz.)

PRINCIPAL DISPLAY PANEL - 30 mL Bottle Carton - Delicate Ivory

NU SKIN®

Nu Colour®

advanced
liquid finish

broad spectrum
SPF 15

30 ml e (1.0 fl. oz.)

PRINCIPAL DISPLAY PANEL - 30 mL Bottle Carton - Honey Beige

NU SKIN®

Nu Colour®

advanced
liquid finish

broad spectrum
SPF 15

30 ml e (1.0 fl. oz.)

PRINCIPAL DISPLAY PANEL - 30 mL Bottle Carton - Medium Beige

NU SKIN®

Nu Colour®

advanced
liquid finish

broad spectrum
SPF 15

30 ml e (1.0 fl. oz.)

PRINCIPAL DISPLAY PANEL - 30 mL Bottle Carton - Medium Ochre

NU SKIN®

Nu Colour®

advanced
liquid finish

broad spectrum
SPF 15

30 ml e (1.0 fl. oz.)

PRINCIPAL DISPLAY PANEL - 30 mL Bottle Carton - Mocha

NU SKIN®

Nu Colour®

advanced
liquid finish

broad spectrum
SPF 15

30 ml e (1.0 fl. oz.)

PRINCIPAL DISPLAY PANEL - 30 mL Bottle Carton - Neutral Beige

NU SKIN®

Nu Colour®

advanced
liquid finish

broad spectrum
SPF 15

30 ml e (1.0 fl. oz.)

PRINCIPAL DISPLAY PANEL - 30 mL Bottle Carton - Ochre

NU SKIN®

Nu Colour®

advanced
liquid finish

broad spectrum
SPF 15

30 ml e (1.0 fl. oz.)

PRINCIPAL DISPLAY PANEL - 30 mL Bottle Carton - Pink

NU SKIN®

Nu Colour®

advanced
liquid finish

broad spectrum
SPF 15

30 ml e (1.0 fl. oz.)

PRINCIPAL DISPLAY PANEL - 30 mL Bottle Carton - Pink Ochre

NU SKIN®

Nu Colour®

advanced
liquid finish

broad spectrum
SPF 15

30 ml e (1.0 fl. oz.)

PRINCIPAL DISPLAY PANEL - 30 mL Bottle Carton - Soft Beige

NU SKIN®

Nu Colour®

advanced
liquid finish

broad spectrum
SPF 15

30 ml e (1.0 fl. oz.)

PRINCIPAL DISPLAY PANEL - 30 mL Bottle Carton - Sunny Beige

NU SKIN®

Nu Colour®

advanced
liquid finish

broad spectrum
SPF 15

30 ml e (1.0 fl. oz.)

PRINCIPAL DISPLAY PANEL - 30 mL Bottle Carton - Sunset Beige

NU SKIN®

Nu Colour®

advanced
liquid finish

broad spectrum
SPF 15

30 ml e (1.0 fl. oz.)

PRINCIPAL DISPLAY PANEL - 30 mL Bottle Carton - Tawny

NU SKIN®

Nu Colour®

advanced
liquid finish

broad spectrum
SPF 15

30 ml e (1.0 fl. oz.)